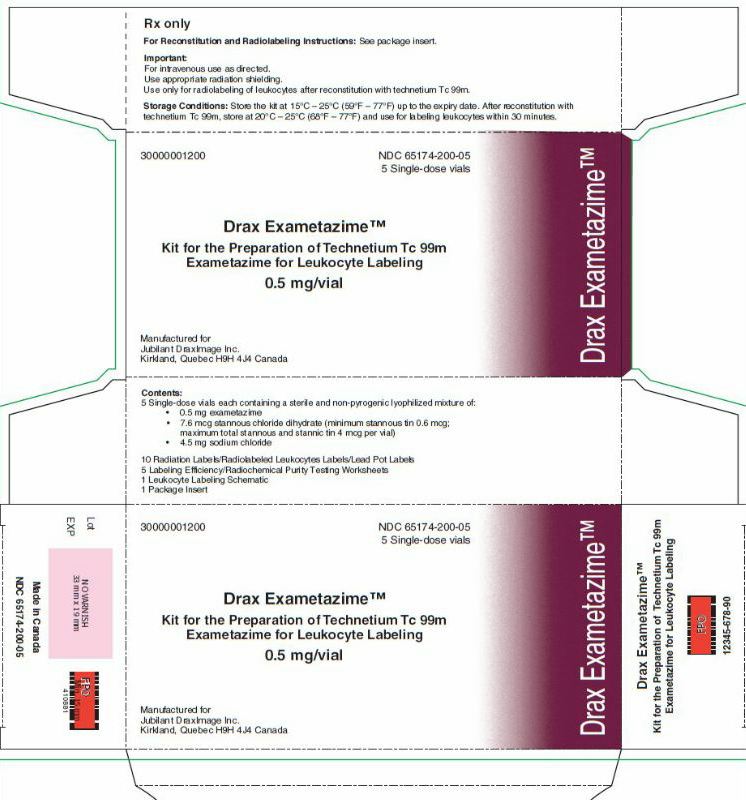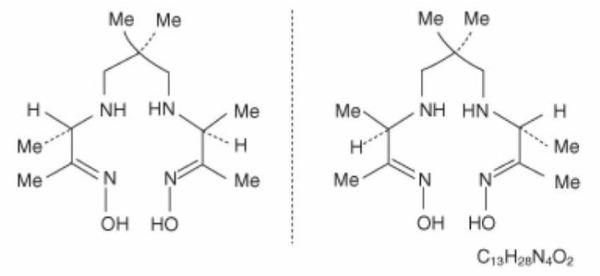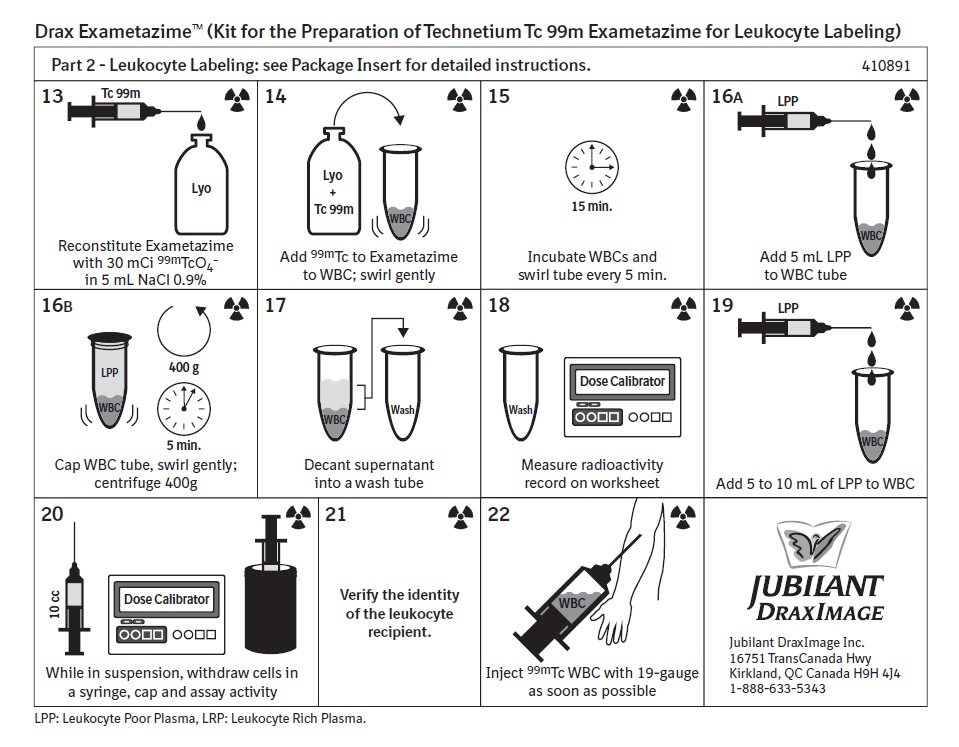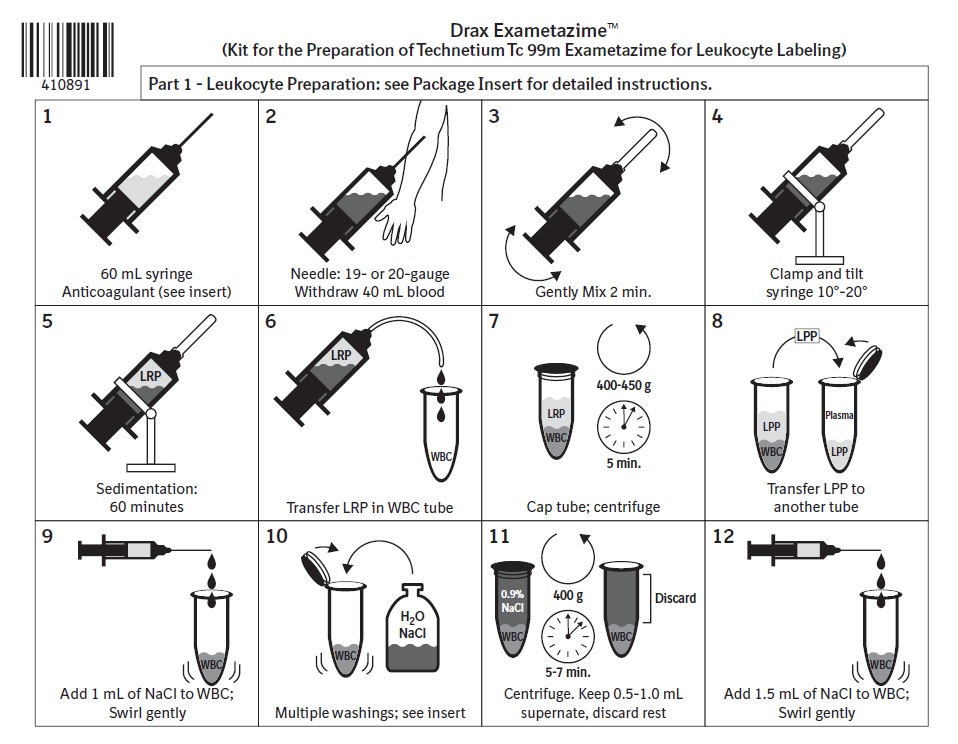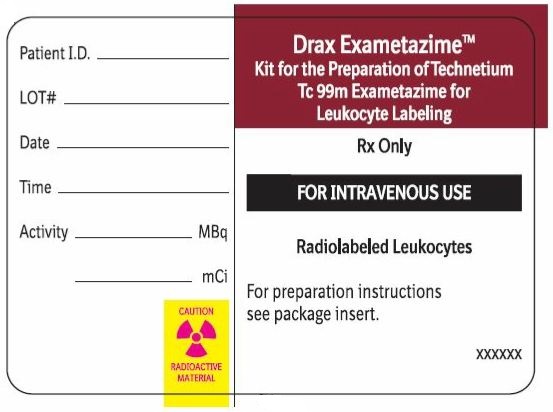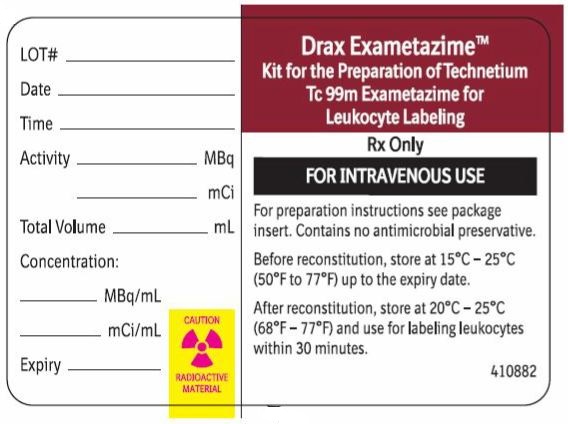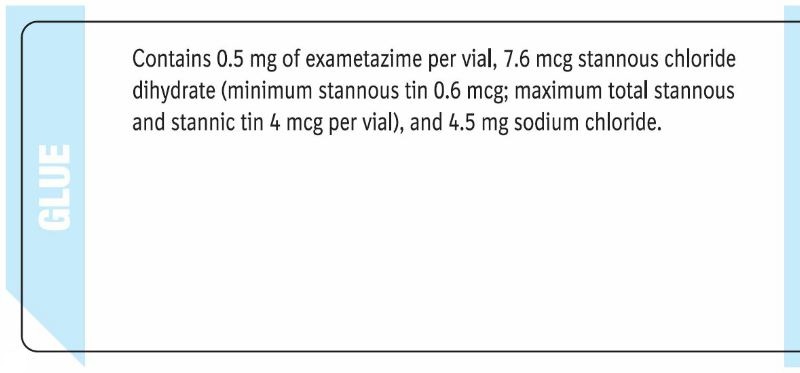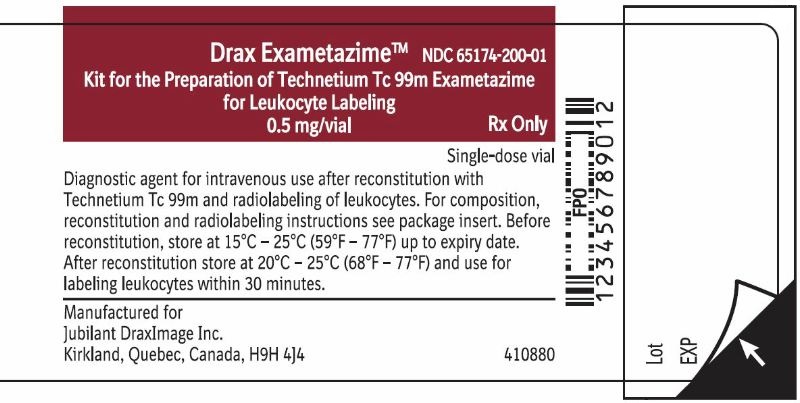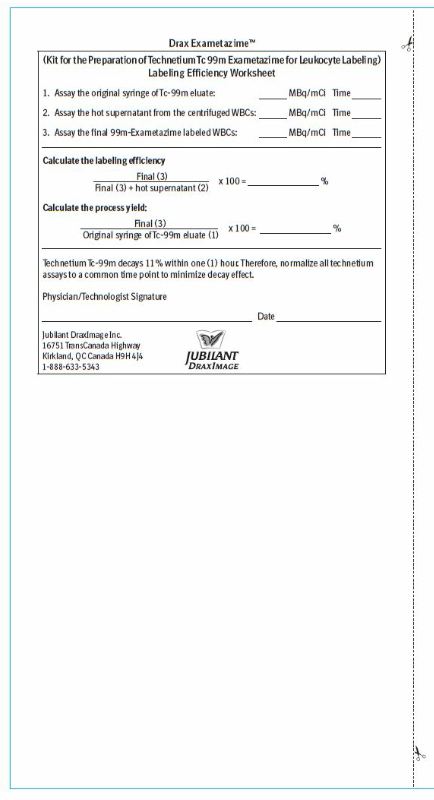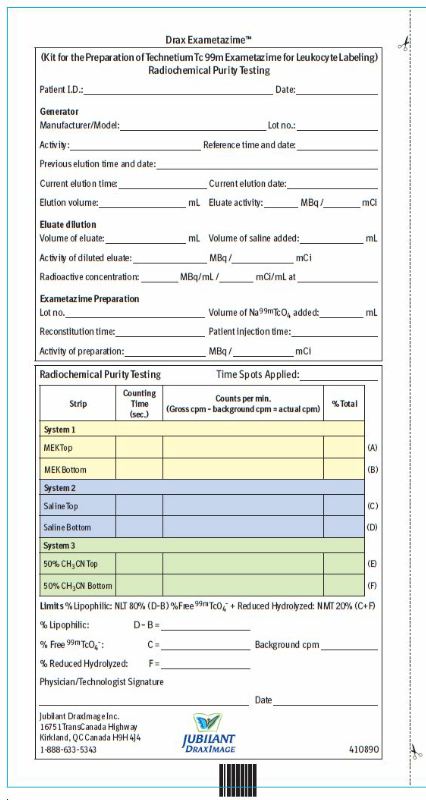 DRUG LABEL: Drax Exametazime
NDC: 65174-200 | Form: INJECTION, POWDER, LYOPHILIZED, FOR SOLUTION
Manufacturer: Jubilant DraxImage Inc., dba Jubilant Radiopharma
Category: prescription | Type: Human Prescription Drug Label
Date: 20241202

ACTIVE INGREDIENTS: TECHNETIUM TC-99M EXAMETAZIME 0.5 mg/1 1
INACTIVE INGREDIENTS: STANNOUS CHLORIDE; SODIUM CHLORIDE; NITROGEN

HIGHLIGHTS OF PRESCRIBING INFORMATION

These highlights do not include all the information needed to use Drax Exametazime safely and effectively. See full prescribing information for Drax Exametazime.
Drax Exametazime (kit for the preparation of technetium Tc 99m exametazime for leukocyte labeling) for intravenous use.
Initial U.S. Approval: 1988

1 INDICATIONS AND USAGE

Drax Exametazime is a radioactive diagnostic agent indicated for leukocyte (white blood cell) labeled scintigraphy as an adjunct in the localization of intra-abdominal infection and inflammatory bowel disease. (1)

2 DOSAGE AND ADMINISTRATION

- Use careful handling with appropriate safety measures to minimize radiation exposure to both patients and healthcare professionals. (2.1)
- For an adult patient, recommended dose is 259 - 925 megabecquerels (MBq) [7-25 millicuries (mCi)]. (2.3)

3 DOSAGE FORMS AND STRENGTHS

Five (5) single-dose vials, each vial contains: 370 MBq up to 2000 MBq (10 mCi up to 54 mCi) [74 - 370 MBq / mL (2 - 10 mCi / mL)] at time of preparation (reconstitution). (3)

4 CONTRAINDICATIONS

None. (4)

5 WARNINGS AND PRECAUTIONS

- Hypersensitivity Reactions: Hypersensitivity reactions, including serious signs and symptoms of anaphylaxis, following administration of Tc 99m labeled leukocytes prepared using Tc 99m exametazime have been reported. Always have cardiopulmonary resuscitation equipment and personnel available and monitor all patients for hypersensitivity reactions. (5.1)

6 ADVERSE REACTIONS

Most common adverse reactions include transient increase in blood pressure, rash, generalized erythema, facial edema and fever. (6)

To report SUSPECTED ADVERSE REACTIONS, contact Jubilant DraxImage Inc. at 1-888-633-5343 or FDA at 1-800-FDA-1088 or www.fda.gov/medwatch.

8 USE IN SPECIFIC POPULATIONS

- Lactation: Temporarily discontinue breastfeeding. A lactating woman should pump and discard breastmilk for 12 to 24 hours after Technetium Tc 99m Exametazime labeled leukocyte administration. (8.2)
- Renal impairment: Increased radiation exposure in patients with impaired renal function. A reduction in administered Tc 99m can be considered provided adequate numbers of labeled WBCs are administered (8.6)

FULL PRESCRIBING INFORMATION

1 INDICATIONS AND USAGE

Drax Exametazime is indicated for leukocyte (white blood cell) labeled scintigraphy as an adjunct in the localization of intra-abdominal infection and inflammatory bowel disease.

2 DOSAGE AND ADMINISTRATION

2.1 Radiation Safety - Drug Handling

Technetium Tc 99m exametazime is a radioactive solution and should be handled with appropriate safety measures to minimize radiation exposure. During handling use waterproof gloves and effective shielding, including syringe shields [see Warnings and Precautions (5.3)].

2.2 Important Administration Instructions

- Use strict aseptic procedures throughout preparation and handling.
- Visually inspect the reconstituted technetium Tc 99m exametazime solution for particulate matter and discoloration prior to radiolabeling of white blood cells. Do not use the reconstituted solution if there is evidence of particulate matter or discoloration.
- Follow the directions of drug preparation carefully to ensure efficient leukocytes labeling [see Dosage and Administration (2.5, 2.6)].
- Measure patient dose with a suitable radioactivity calibration system immediately prior to administration.
- Instruct patients to hydrate, after administration of technetium Tc 99m exametazime labeled white blood cells and void frequently to minimize radiation dose to the kidneys and bladder [see Warnings and Precautions (5.3)].

2.3 Recommended Dosage and Administration

For an adult patient the recommended intravenous injection dose range for technetium Tc 99m exametazime labeled leukocytes is 259 - 925 Megabecquerels (MBq) [7-25 millicuries (mCi)].

2.4 Image Acquisition and Inerpretation

Acquisition

- Instruct patients to empty their bladder prior to imaging.
- Obtain serial pelvic and abdominal images beginning at 0.5 – 1 hour post-injection and continue up to 4 hours.

Interpretation

- Accumulation of radioactivity in bowel seen in early images [less than 4 hours] with increasing intensity and/or no evidence of changing location secondary to GI motility likely represents inflammatory bowel disease or infection. Radioactivity from hepatic excretion detected in the bowel 4 hours post-injection and changing in GI location on serial/subsequent images is indicative of normal GI transit [see Clinical Pharmacology (12.2)]

2.5 Preparation of Autologous Leukocytes

IMPORTANT - Label all syringes and tubes used in this labeling procedure with the patient’s name and unique identification number.

Leukocyte Harvest and Separation
1. Draw 2 mL of Heparin and 8 mL of 6% Hydroxyethyl starch into a 60 mL plastic syringe.
2. Withdraw approximately 40 mL whole blood from the patient into the syringe using a 19-gauge Butterfly needle infusion set. Close the syringe with a sterile hub.
3. Gently mix the contents for 2 minutes.
4. Clamp the syringe barrel to the ring stand in an upright (hub side up) position and tilt the syringe approximately 10-20 degrees from its position perpendicular to the bench.
5. Allow the syringe to stand a minimum of 60 minutes until the red blood cells sediment and the supernatant looks clear.
6. Using an infusion set, transfer the leukocyte-rich plasma (LRP), the supernatant, from the previous step, into a sterile, conical centrifuge tube marked "WBC" (white blood cell) and assure that only a minimum amount of red cells enter the centrifuge tube.
7. Immediately centrifuge the capped WBC tube at 400-450 g for 5 minutes. The plasma will separate out into a liquid [leukocyte poor plasma (LPP)] and a solid (WBC button). The WBC button often contains a small number of red blood cells and may appear red.
8. Transfer the leukocyte poor plasma (LPP) into another sterile centrifuge tube marked as "Plasma" tube, without disturbing the WBC button. Save the LPP in the Plasma tube for later use (Steps 16 and 19).

Red Blood Cell Lysis and Washing
9. Add 1 mL Sodium Chloride (Na Cl) Injection, USP (0.9%) to the WBC button and suspend.
10. Add the following to the WBC suspension in succession and swirl the centrifuge tube (WBC tube) for 5-30 seconds after each addition. (Attention to timing is important as exposing leukocytes to a hypotonic solution for a prolonged period will damage leukocytes and result in poor leukocyte labeling results):
a) 9 mL sterile water;
b) 2 mL of 5% Na Cl; and
c) 10 mL of 0.9% Na Cl.
11. Cap the WBC tube and centrifuge at 400 g for 5-7 minutes. Draw off the supernatant into the "Waste" tube.
12. Add 1.5 mL of 0.9% Na Cl and re-suspend the WBC button by gentle shaking.
13. Reconstitute technetium Tc 99m exametazime with generator eluate [see Dosage and Administration (2.7)]. Measure the radioactivity and record as item (1) on the Technetium Tc 99m Exametazime Labeling Efficiency Worksheet. Use for radiolabeling WBC within 30 minutes.

2.6 Labeling of Autologous Leukocytes with Technetium Tc 99m Exametazime

14. Carefully add the reconstituted technetium Tc 99m exametazime to the WBC tube containing the WBC button isolated in Step 12.
15. Incubate the WBCs at room temperature for 15 minutes. Swirl during the incubation every 5 minutes.
16. Add 5 mL of LPP (from Step 8) to the WBC tube. Cap the WBC tube and centrifuge at 400 g for 5 minutes.
17. Carefully remove the supernatant and place into the tube labeled “Wash.” Keep the labeled white cells in the WBC tube.
18. Measure the radioactivity of the Wash tube and record as item (2) on the Technetium Tc 99m Exametazime Labeling Efficiency Worksheet.
19. Add 5-10 mL of LPP (from Step 8) to the Tc 99m labeled leukocyte preparation (WBC tube). Gently swirl to mix.
20. Draw up the labeled cells into a non-heparinized syringe with a large bore needle (no smaller than 19-gauge) and cap it with a sterile hub. Measure the radioactivity of the cells and record as item (3) on the Technetium Tc 99m Exametazime Labeling Efficiency Worksheet.
21. Verify the identity of the leukocyte recipient.
22. Labeled cells are now ready for administration. Administer as soon as possible and preferably within 1-2 hours after labeling.
23. Calculate the labeling efficiency from the Labeling Efficiency Worksheet:

Radioactivity of the cells [item (3)]
Radioactivity of the cells [item (3)] + activity in the supernatant [item (2)]

Labeling efficiency >50% is anticipated.

2.7 Preparation of Technetium Tc 99m Exametazime

The technetium Tc 99m labeling reaction involved in preparing the agent depends on maintaining the stannous ion in the reduced state. Any oxidant present in the sodium pertechnetate Tc 99m may adversely affect the radiolabeling efficiency.

- Elute the Tc 99m generator according to the manufacturer’s instructions.
  - Use only eluate from a Tc 99m generator which was eluted within the previous 24 hours.
  - Prepare the technetium Tc99m exametazime with eluate that is not more than 2 hours old.
- Add 370 MBq up to 2000 MBq (10 mCi up to 54 mCi) sodium pertechnetate Tc 99m to Drax Exametazime vial.
- Before reconstitution, add up to 5 mL preservative-free, non-bacteriostatic Sodium Chloride Injection USP (0.9%) to the generator eluate to achieve a radioactive concentration no greater than 74-370 MBq/mL (2-10 mCi/mL).
- Measure the radioactivity and record as item (1) on the Technetium Tc 99m Exametazime Labeling Efficiency Worksheet.
- Use a sample for Quality Control [see Dosage and Administration (2.8)].
- Maintain reconstituted product at 20°C - 25°C (68°F - 77°F).
- Use for WBC labeling within 30 minutes.
- Discard any unused material according to local radiation safety procedures.

2.8 Radiochemical Purity Testing - Quality control of Tc 99m Exametazime

Obtain the Following Materials:
SG ITLC strips 6 cm x 0.7 cm
Whatman Grade 31ET chromatographic paper strip 6 cm x 0.7 cm
MEK (methyl ethyl ketone [butanone]) (99.9 + % HPLC Grade)
0.9% aqueous sodium chloride (non-bacteriostatic)
50% aqueous acetonitrile (99.9 + % HPLC Grade)
Glass test tubes (12 x 75 mm) with covers
1 mL syringes with 25-gauge needles.
Collimated radiation detector.

- Perform radiochemical purity testing of technetium Tc 99m exametazime before leukocyte labeling and within 2 minutes of reconstitution.
- This entire radiochemical purity testing procedure takes approximately 15 minutes.
- A combination of 3 chromatographic systems is necessary for the complete definition of the radiochemical composition of the injection.
  - System 1: methyl ethyl ketone (MEK) + SG ITLC strip
  - System 2: 0.9% non-bacteriostatic sodium chloride solution + SG ITLC strip
  - System 3: 50% acetonitrile solution + Whatman 31ET paper strip
- Three potential radiochemical impurities may be present in the prepared injection of the lipophilic Tc 99m exametazime complex:
  - secondary Tc 99m exametazime complex
  - free Tc 99m pertechnetate
  - reduced-hydrolyzed Tc 99m

Method
1. Prepare three chromatographic systems using 12 mm × 75 mm chromatographic tubes with the following solvents (identify the solvent in each tube):
System 1- 0.3 mL of fresh methyl ethyl ketone (MEK),
System 2 - 0.9% non-bacteriostatic sodium chloride solution,
System 3 - 50% acetonitrile solution, prepared with non-bacteriostatic water
2. Apply 5 µL of freshly prepared Tc 99m exametazime solution (within 2 minutes of reconstitution) about 1 cm from the bottom of three strips: two 6cm × 0.7cm instant thin-layer chromatographic strips and one 6 cm × 0.7cm strip of chromatographic paper. Do not allow to dry.
3. Place one SG ITLC strip into the MEK tube (System 1), the second SG ITLC strip into the saline tube (System 2) and the Whatman 31ET paper strip into the 50% acetonitrile tube (System 3). Make sure strips are not adhering to the sides of the tube.
4. Allow the chromatograms to develop until the solvent front has moved to the top of the strips. Remove the strips from the tubes, and allow the solvents to evaporate.
5. Determine the radioactive distribution by scanning the strip sections, using a suitable collimated radiation detector.

Chromatogram Interpretation
6. Using the Radiochemical Purity Worksheet, record the following counts:

System 1 (SG ITLC: MEK [butanone])
Migrate at Rf 0.8-1 | Lipophilic Tc 99m exametazime complex and Tc 99m pertechnetate
Origin | Secondary Tc 99m exametazime complex and reduced-hydrolyzed Tc 99m.

System 2 (SG ITLC: 0.9% sodium chloride)
Migrate at Rf 0.8-1 | Tc 99m pertechnetate
Origin | Lipophilic Tc 99m exametazime complex, secondary Tc 99m exametazime complex and reduced- hydrolyzed Tc 99m

System 3 (Whatman 31ET: 50% aqueous acetonitrile)
Migrate at Rf 0.8-1 | Lipophilic Tc 99m exametazime complex, secondary Tc 99m exametazime complex and Tc 99m pertechnetate
Origin | Reduced-hydrolyzed Tc 99m

7. Determine and record on the Radiochemical Purity Worksheet:
% at the origin of saline strip (D)
% at the origin of MEK strip (B)
% at the solvent front of saline strip (C) [% Tc 99m pertechnetate]
% at the origin of Whatman 31ET paper strip (F) [% reduced-hydrolyzed Tc 99m]

8. Calculate the radiochemical purity:
% lipophilic exametazime complex = % at the origin of saline strip (D) – % at the origin of MEK strip (B)

9. Do not use if radiochemical purity of Lipophilic Tc 99m Exametazime is less than 80%

2.9 Radiation Dosimetry

Based on human data, the radiation absorbed doses in an adult patient from an intravenous injection of Tc 99m labeled leukocytes have been estimated and are provided in Table 1.

Table 1 Tc 99m Exametazime Labeled Leukocytes
Organ | Absorbed dose per unit activity administered | Absorbed dose per unit activity administered
 | (microGy/MBq) | (mrad/mCi)
Spleen | 88 | 327
Red marrow | 15 | 54
Liver | 13 | 48
Bone surfaces | 8.4 | 31
Urinary bladder | 8.2 | 30
Lungs | 7.4 | 27
Stomach | 6.7 | 25
Upper large intestine | 5.5 | 20
Colon | 4.5 | 17
Lower large intestine | 3.3 | 12
Small intestine | 2.5 | 9.3
Ovaries | 1.6 | 6
Thyroid | 1.3 | 4.8
Breast | 0.9 | 3.3
Testes | 0.8 | 3
Kidneys | 0.3 | 1.1
Remaining organs | 2.2 | 8.1
Effective dose per administered activity | 7.5 microSv/MBq | 28 mrem/mCi

3 DOSAGE FORMS AND STRENGTHS

Drax Exametazime is a kit containing five (5) single-dose vials. Each 10 mL, clear glass vial contains a non-radioactive lyophilized mixture of: 0.5 mg exametazime, 7.6 mcg stannous chloride dihydrate (minimum stannous tin 0.6 mcg; maximum total stannous and stannic tin 4 mcg per vial) and 4.5 mg sodium chloride, sealed under nitrogen atmosphere with a rubber closure.

When reconstituted with the technetium Tc 99m eluate, each vial will contain a clear, colorless, and foreign particles-free solution of 370 MBq up to 2000 MBq (10 mCi up to 54 mCi) [74 - 370 MBq / mL (2 - 10 mCi / mL)]. The radioactive solution produced will be used for leukocyte labeling before intravenous administration to the patient.

4 CONTRAINDICATIONS

None.

5 WARNINGS AND PRECAUTIONS

5.1 Hypersensitivity Reactions

Hypersensitivity reactions, including serious signs and symptoms of anaphylaxis, following administration of Tc 99m labeled leukocytes prepared using Tc 99m exametazime have been reported. Always have cardiopulmonary resuscitation equipment and personnel available and monitor all patients for hypersensitivity reactions.

5.2 Risk for Image Interpretation Error

The interpretation of images can be affected by the presence of other pathophysiological processes within and outside of the abdominal cavity such as: tumor, infarction, trauma, and other inflammatory conditions.

5.3 Radiation Exposure Risk

Technetium Tc 99m contributes to a patient’s overall long-term cumulative radiation exposure. Long-term cumulative radiation exposure is associated with an increased risk of cancer. Ensure safe handling and preparation reconstitution procedures to protect patients and health care workers from unintentional radiation exposure. Encourage patients to drink fluids and void as frequently as possible after administration [see Dosage and Administration (2.1,2.2)].

6 ADVERSE REACTIONS

The following adverse reactions are described elsewhere in the labeling;

- Hypersensitivity reactions [see Warnings and Precautions (5.1)].

The following adverse reactions associated with the use of technetium Tc 99m exametazime have been identified in clinical trials or post-marketing reports. Because these reactions are reported voluntarily from a population of uncertain size, it is not always possible to reliably estimate their frequency or establish a causal relationship to drug exposure.

- Cardiovascular: transient blood pressure increase
- Skin and subcutaneous tissue disorders: rash, generalized erythema, urticaria, angioedema, pruritus.
- General disorders and administration site conditions: facial edema, fever, asthenic conditions (e.g., malaise, fatigue).
- Nervous system disorders: headache, dizziness, paraesthesia.
- Vascular disorders: flushing.
- Gastrointestinal disorders: nausea, vomiting.

8 USE IN SPECIFIC POPULATIONS

8.1 Pregnancy

Risk Summary
Limited available data with technetium Tc 99m exametazime use in pregnant women are insufficient to inform a drug associated risk for major birth defects and miscarriage. Technetium Tc 99m exametazime is transferred across the placenta [see Data]. Animal reproduction studies with technetium Tc 99m exametazime have not been conducted. However, all radiopharmaceuticals have the potential to cause fetal harm depending on the fetal stage of development and the magnitude of the radiation dose. If considering technetium Tc 99m exametazime administration to a pregnant woman, inform the patient about the potential for adverse pregnancy outcomes based on the radiation dose from technetium Tc 99m exametazime and the gestational timing of exposure.

The estimated background risk of major birth defects and miscarriage for the indicated population is unknown. All pregnancies have a background risk of birth defect, loss, or other adverse outcomes. In the U.S. general population, the estimated background risk of major birth defects and miscarriage in clinically recognized pregnancies are 2-4% and 15-20%, respectively.

Data
Human Data
Limited published literature describes Tc-99m exametazime crossing the placental barrier and accumulating in the fetal liver. No adverse fetal effects or radiation-related risks have been identified for diagnostic procedures involving less than 50mGy, which represents less than 10mGy fetal doses.

8.2 Lactation

Risk Summary
There are limited data available in the scientific literature on the presence of technetium Tc 99m exametazime in human milk. There no data available on the effects of technetium Tc 99m exametazime on the breastfed infant or the effects on milk production. Exposure of technetium Tc 99m exametazine to a breast fed infant can be minimized by temporary discontinuation of breastfeeding [see Clinical Considerations]. The developmental and health benefits of breastfeeding should be considered along with the mother’s clinical need for technetium Tc 99m exametazime, any potential adverse effects on the breastfed child from technetium Tc 99m exametazime or from the underlying maternal condition.

Clinical Considerations
To decrease radiation exposure to the breastfed infant, advise a lactating woman to pump and discard breast milk after the administration of technetium Tc 99m exametazime-labeled leukocytes for 12 to 24 hours, where the duration corresponds to the typical range of administered activity, 259 MBq to 925 MBq (7 mCi to 25 mCi).

8.4 Pediatric Use

Safety and efficacy in pediatric patients have not been assessed.

8.6 Renal Impairment

Technetium Tc 99m exametazime is substantially excreted by the kidneys, so excretion is decreased / delayed and therefore radiation exposure is greater in patients with impaired renal function. A reduction in administered Tc 99m can be considered provided an adequate number of labeled WBCs are administered.

8.5 Geriatric Use

Clinical studies of Tc 99m exametazime did not include sufficient numbers of subjects aged 65 and over to determine whether they respond differently from younger subjects. Other reported clinical experience has not identified differences in responses between the elderly and younger patients. In general, dose selection for an elderly patient should be cautious, usually starting at the low end of the dosing range, reflecting the greater frequency of decreased hepatic, renal or cardiac function, and of concomitant disease or other drug therapy.

10 OVERDOSAGE

In the event of the administration of a radiation overdose, hydration and frequent micturition should be encouraged in order to minimize the absorbed dose to patient.

11 DESCRIPTION

11.1 Chemical Characteristics

Drax Exametazime (kit for the preparation of technetium Tc 99m exametazime for leukocyte labeling) prepares a radioactive diagnostic agent. Each single-dose vial contains a sterile, non-pyrogenic, lyophilized mixture of 0.5 mg exametazime, 7.6 mcg stannous chloride dihydrate (minimum stannous tin 0.6 mcg; maximum total stannous and stannic tin 4 mcg per vial) and 4.5 mg sodium chloride, sealed under nitrogen atmosphere with a rubber closure. The product contains no antimicrobial preservative.
The chemical formula of exametazime is C13H28N4O2, with the following structural formula:

Prior to publication of the USAN, exametazime [also known as (RR,SS)-4.8-diaza-3,6,6,9-tetramethylundecane-2, 10-dione bisoxime] was known as hexamethylpropylene amine oxime (HM-PAO). The name HM-PAO appears in many publications.

When Tc 99m pertechnetate in Sodium Chloride Injection, USP (0.9%) is added to Drax Exametazime vial, a Tc 99m complex of exametazime is formed.

11.2 Physical Characteristics

Tc 99m decays by isomeric transition with a physical half-life of 6 hours. Photons that are useful for imaging studies are listed in Table 2.

Table 2 Principal Radiation Emission Data - Tc 99m
Radiation | Mean %/Disintegration | Mean Energy (keV)
Gamma 2 | 88.5 | 140.5

11.3 External Radiation

The air-kerma-rate (exposure-rate) constant for technetium Tc 99m is 5.23 m^2·pGy·(MBq)^-1·s^-1 [0.795 cm^2·R·(mCi)^-1·h^-1]. The first half-value thickness of lead (Pb) for Tc 99m is 0.25 mm. A range of values for the relative attenuation of the radiation emitted by this radionuclide that results from interposition of various thicknesses of Pb is shown in Table 3. For example, the use of a 3 mm thickness of Pb will decrease the external radiation exposure by a factor of approximately 1,000.

Table 3 Radiation Attenuation by Lead Shielding
Shield Thickness (Pb) mm | Coefficient of Attenuation
0.25 | 0.5
1 | 10^-1
2 | 10^-2
3 | 10^-3
4 | 10^-4
5 | 10^-5

To correct for physical decay of this radionuclide, the fractions that remain at selected intervals relative to the time of calibration are shown in Table 4.

Table 4 Physical Decay Chart - Tc 99m half-life 6 hours
Hours | Fraction Remaining | Hours | Fraction Remaining
0 [Calibration time (time of preparation)] | 1.00 | 7 | 0.45
1 | 0.89 | 8 | 0.4
2 | 0.79 | 9 | 0.35
3 | 0.71 | 10 | 0.32
4 | 0.63 | 11 | 0.28
5 | 0.56 | 12 | 0.25
6 | 0.50 | 24 | 0.063

12 CLINICAL PHARMACOLOGY

12.1 Mechanism of Action

When technetium Tc 99m pertechnetate is added to exametazime in the presence of stannous reductant, a lipophilic technetium Tc 99m complex is formed. This lipophilic complex is the active moiety. The lipophilic technetium Tc 99m exametazime complex is taken up and retained in leukocytes.

12.2 Pharmacodynamics

The relationship between technetium Tc 99m exametazime labeled WBC concentrations and successful imaging was not explored in clinical trials. GI activity is typically not seen through the initial four (4) hours post-injection. By four (4) hours, the hepatobiliary excretion of the Tc 99m exametazime allows tracer (Tc 99m) accumulation in the hepatobiliary system and, hence bowel activity.

12.3 Pharmacokinetics

Distribution

During the first hour following the injection, radioactivity is seen in the lungs, liver, gall bladder, spleen, blood pool, bone marrow, kidneys, and bladder. Over the first 1-6 hours, the Tc 99m is visualized in the bowel. At 24 hours post-injection substantial colonic activity is seen. The normal areas visualized in earlier scans are still visible.

Elimination

Excretion
Tc 99m excretion occurs via urine and feces.

14 CLINICAL STUDIES

Two clinical trials of technetium Tc 99m exametazime were performed in a total of 88 patients who had suspected intra-abdominal infection or inflammation. Subjects received both Tc 99m labeled leukocytes and a radiolabeled comparator. Images were obtained at 2 and 30 minutes and at 2, 4 and 24 hours. In two other clinical trials, a total of 127 patients with suspected abdominal inflammation or infection received Tc 99m labeled leukocytes. Imaging was at 24 hours in one study and at 1, 3 and 24 hours in the other. In all four studies images were blindly evaluated and the findings were confirmed by surgery, biopsy or other clinical data.

Based on the above 4 studies, between 2 to 4 hours Tc 99m labeled leukocytes had 95-100% sensitivity and 62-85% specificity. In all studies the false positive and false negatives relate to the bowel background, the location of the site of infection/inflammation and whether or not it is contiguous with the bowel. Images obtained at 24 hours can be unreliable because of a high bowel background.

The interpretation of the images could also be affected by the presence of tumors, infarction and peritonitis [See Warning and Precautions (5.2)]. Liver abscess may be missed in planar imaging because of the bowel background.

16 HOW SUPPLIED/STORAGE AND HANDLING

16.1 How Supplied

Drax Exametazime kit (NDC 65174-200-05) comprises:

- 5 Single-dose vials (0.5 mg/vial). Each vial contains a non-radioactive sterile, non-pyrogenic lyophilized mixture of: 0.5 mg of exametazime, 7.6 mcg stannous chloride dihydrate, and 4.5 mg sodium chloride (NDC 65174-200-01);
- 10 Radiation Labels/Radiolabeled Leukocytes Labels/Lead Pot Labels ;
- 5 Labeling Efficiency/Radiochemical Purity Testing Worksheets;
- 1 Leukocyte Labeling Schematic;
- 1 Package Insert.

Sodium Pertechnetate Tc 99m is not part of Drax Exametazime kit. Before reconstitution and radiolabeling with Tc 99m, the contents of the kit are not radioactive.

16.2 Storage and Handling

Store Drax Exametazime kit at 15°C - 25°C (59°F - 77°F).
Drax Exametazime is for distribution to and use by persons licensed authorized by the U.S. Nuclear Regulatory Commission or the relevant regulatory authority of an Agreement State. Store and dispose of technetium Tc 99m exametazime in compliance with the appropriate regulations of the government agency authorized to license the use of this radionuclide.

17 PATIENT COUNSELING INFORMATION

Administration Instructions:

- Advise patients to hydrate after administration of technetium Tc 99m exametazime labeled leukocytes and to void frequently to minimize radiation dose [see Dosage and Administration (2.2)].

Pregnancy

- Advise pregnant women of the risk of fetal exposure to radiation doses if they undergo a radionuclide procedure [see Use in Specific Populations (8.1)].

Lactation

- Advise lactating women that exposure of the infant to technetium Tc 99m through breast milk can be minimized if breastfeeding is interrupted when technetium Tc99m exametazime labeled leukocytes are administered. Advise a lactating woman to pump and discard breast milk for 12 to 24 hours based on injected dose [see Use in Specific Populations (8.2)].

Manufactured for:
Jubilant DraxImage Inc., Kirkland, Quebec, Canada, H9H 4J4.

Art rev.: 1.0

Carton Label

Rx only
For Reconstitution and Radiolabelling Instructions:See package insert.

Important: For intravenous use as directed.
Use appropriate radiation shielding.
Use only for radiolabeling of leukocytes after reconstitution with technetium Tc 99m.

Storage Conditions: Store the kit at 15°C-25°C (59°F-77°F) up to the expiry date. After reconsitution with technetium Tc 99m, store at 20°C-25°C (68°F-77°F) and use for labeling leukocytes within 30 minutes.

NDC 65174-200-05
5 single dose vials

Drax Exametazime
Kit for the Preparation of Technetium Tc 99m
Exametazime for Leukocyte Labeling
0.5 mg/vial

Manufactured for
Jubilant DraxImage Inc.
Kirkland, Quebec H9H 4J4 Canada

Contents: 5 single-dose vials each containing a sterile and non-pyrogenic lyophilized mixture of:

- 0.5 mg exametazime
- 7.6 mcg stannous chloride dihydrate (minimum stannous tin 0.6 mcg; maximum total stannous and stannic tin 4mcg per vial)
- 4.5 mg sodium chloride

10 Radiation Labels/Radiolabeled Leukocyte Labels/Lead Pot Labels
5 Labeling Efficiency/Radiochemical Purity Testing Worksheets
1 Leukocyte Labeling Schematic
1 Package Insert

Made in Canada

Vial Label

Drax Exametazime
Kit for the Preparation of Technetium Tc 99m Exametazime
for Leukocyte Labeling
0.5 mg/vial

NDC 65174-200-01
Rx Only

Single-dose vial
Diagnostic agent for intravenous use after reconstitution with Technetium Tc 99m and radiolabeling of leukocytes. For composition, reconstitution and radiolabeling instructions see package insert. Before reconstitution, store at 15°C-25°C (59°F-77°F) up to expirty date. After reconstitution store at 20°C-25°C (68°F-77°F) and use for labeling leukocytes within 30 minutes.

Manufactured for
Jubilant DraxImage Inc.
Kirkland, Quebec, Canada H9H 4J4

Contains 0.5 mg of exametazime per vial, 7.6 mcg stannous chloride dihydrate (minimum stannous tin 0.6 mcg; maximum total stannous and stannic tin 4 mcg per vial), and 4.5 mg sodium chloride.

Radiation Label

Drax Exametazime
Kit for the Preparation of Technetium
Tc 99m Exametazime for Leukocyte Labeling
Rx Only
FOR INTRAVENOUS USE

For preparation instructions see package insert. Contains no antimicrobial preservative.
Before reconstitution, store at 15°C-25°C (59°F-77°F) up to expiry date.
After reconstitution store at 20°C-25°C (68°F-77°F) and use for labeling leukocytes within 30 minutes.

Radiolabeled Leukocyte Lead Pot Label

Drax Exametazime
Kit for the Preparation of Technetium
Tc 99m Exametazime for Leukocyte Labeling
Rx Only
FOR INTRAVENOUS USE

Radiolabled Leukocytes

For preparation instructions see package insert.

Labeling Schematic

Drax Exametazime (Kit for the Preparation of Technetium Tc 99m Exametazime for Leukocyte Labeling)

Leukocyte Preparation: see Package Insert for detailed instructions.

1. 60 mL syringe
  Anticoagulant (see insert)
2. Needle: 19- or 20-gauge
  Withdraw 40mL blood
3. Gently Mix 2 min.
4. Clamp and tilt syringe 10°-20°
5. Sedimentation: 60 minutes
6. Transfer LRP in WBC tube
7. Cap tube; centrifuge
8. Transfer LPP to another tube
9. Add 1 mL of NaCl to WBC;
  Swirl gently
10. Multiple washings; see insert
11. Centrifuge. Keep 0.5-1.0 mL supernate, discard rest
12. Add 1.5 mL of NaCl to WBC;
  Swirl gently
13. Reconstitute Exametazime with 30mCi99mTcO4^- in 5 mL NaCl 0.9%
14. Add 99mTc to Exametazime to WBC; swirl gently
15. Incubate WBCs and swirl tube every 5 min.
16. Add 5 mL LPP to WBC tube
  Cap WBC tube, swirl gently; centrifuge 400g
17. Decant supernatant into a wash tube
18. Measure radioactivity record on worksheet
19. Add 5 to 10 mL of LPP to WBC
20. While in suspension, withdraw cells in a syringe, cap and assay activity
21. Verify the identity of the leukocyte recipient.
22. Inject 99mTc WBC with 19-gauge as soon as possible

Jubilant DraxImage Inc.
16751 TransCanada Hwy
Kirkland, QC Canada H9H 4J4
1-888-633-5343

LPP: Leukocyte Poor Plasma, LRP: Leukocyte Rich Plasma

RCP Efficiency Worksheets